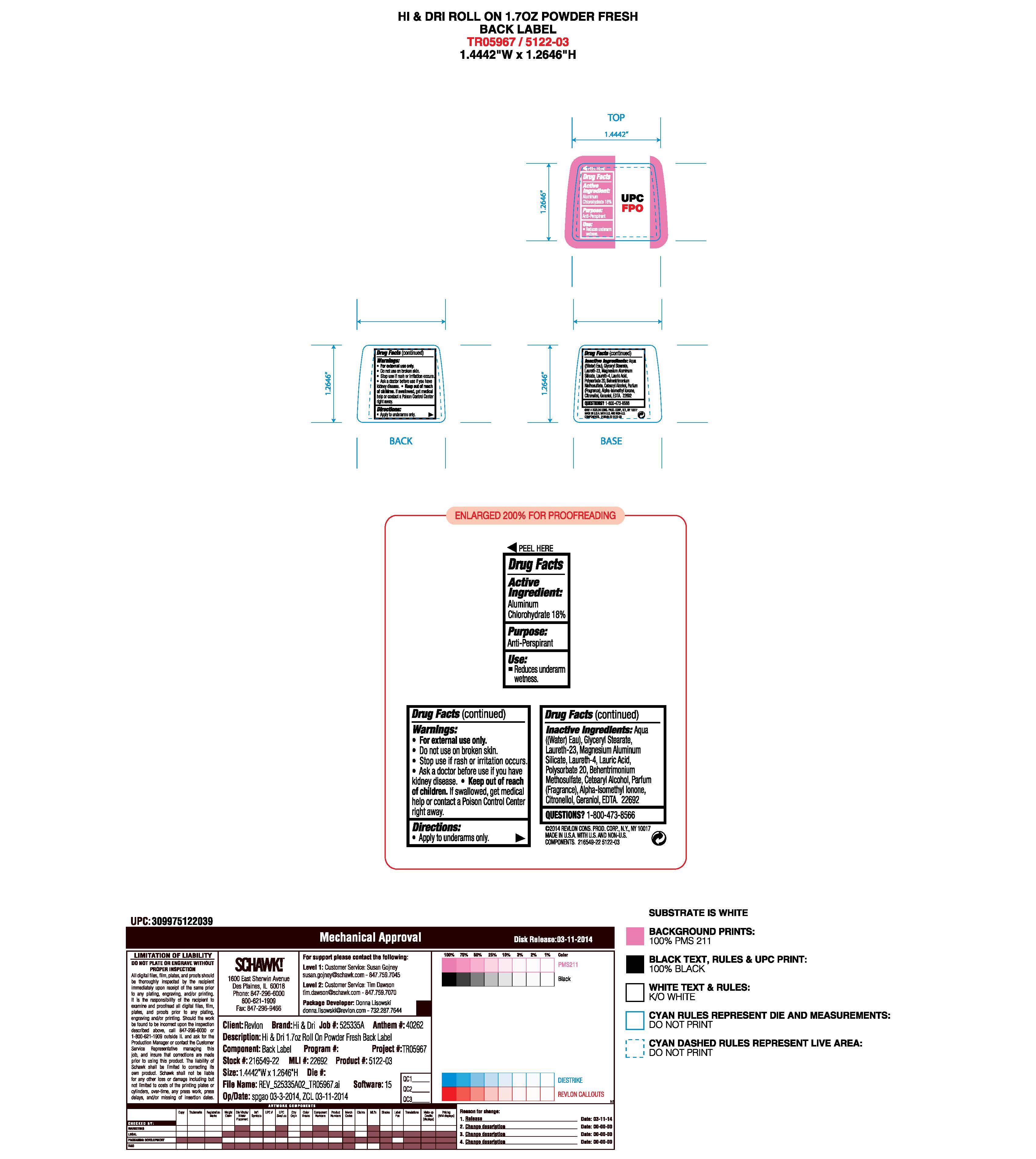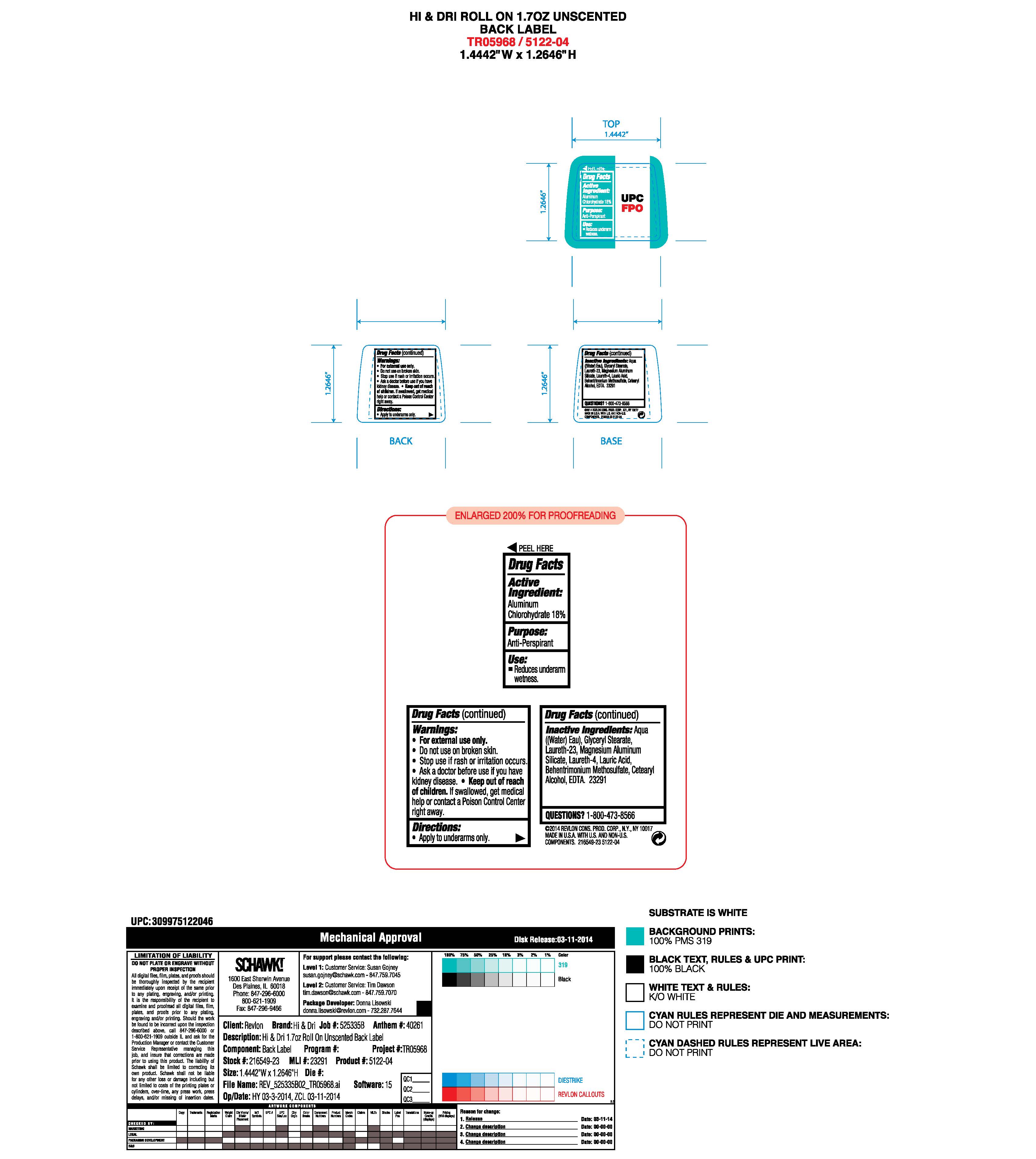 DRUG LABEL: Hi and Dri Roll On
NDC: 10967-786 | Form: LIQUID
Manufacturer: Revlon Consumer Products Corp
Category: otc | Type: HUMAN OTC DRUG LABEL
Date: 20241231

ACTIVE INGREDIENTS: ALUMINUM CHLOROHYDRATE 0.18 g/1 mL
INACTIVE INGREDIENTS: WATER; MAGNESIUM ALUMINUM SILICATE; LAURETH-4; LAURIC ACID; CETEARYL ALCOHOL; BEHENTRIMONIUM METHOSULFATE; EDTA; GLYCERYL MONOSTEARATE; LAURETH-23; POLYSORBATE 20

Hi & Dri Antiperspirant Roll-On - Powder Fresh

ACTIVE INGREDIENT

Aluminum chlorohydrate 18%

Purpose

Antiperspirant

Warnings:

For external use only.

Do not use on broken skin

Ask a doctor before use if you have kidney disease

Stop use if rash or irriation occurs

KEEP OUT OF REACH OF CHILDREN

If swallowed, get medical help or contact a Poison Control Center right away.

Inactive Ingredients

aqua((water) eau), glyceryl stearate, laureth-23, magnesium aluminum silicate, laureth-4, lauric acid, cetearyl alcohol, behentrimonium methosulfate, edta

INDICATIONS AND USAGE

Reduces underarm wetness

PACKAGE LABEL

Hi & Dri Roll-On Antiperspirant